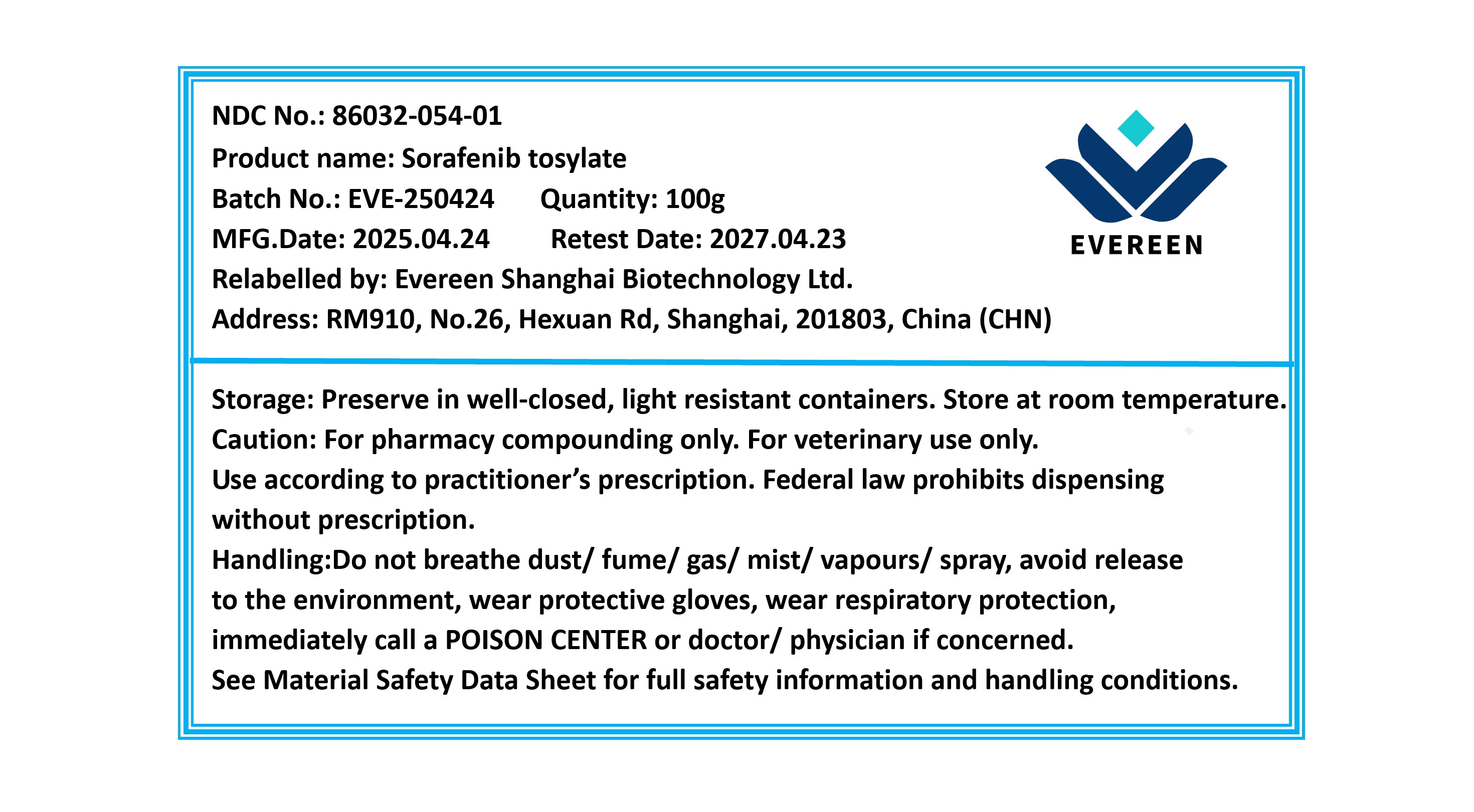 DRUG LABEL: Sorafenib tosylate
NDC: 86032-054 | Form: POWDER
Manufacturer: Evereen Shanghai Biotechnology Ltd.
Category: other | Type: BULK INGREDIENT - ANIMAL DRUG
Date: 20250722

ACTIVE INGREDIENTS: SORAFENIB TOSYLATE 1 g/1 g

Sorafenib tosylate